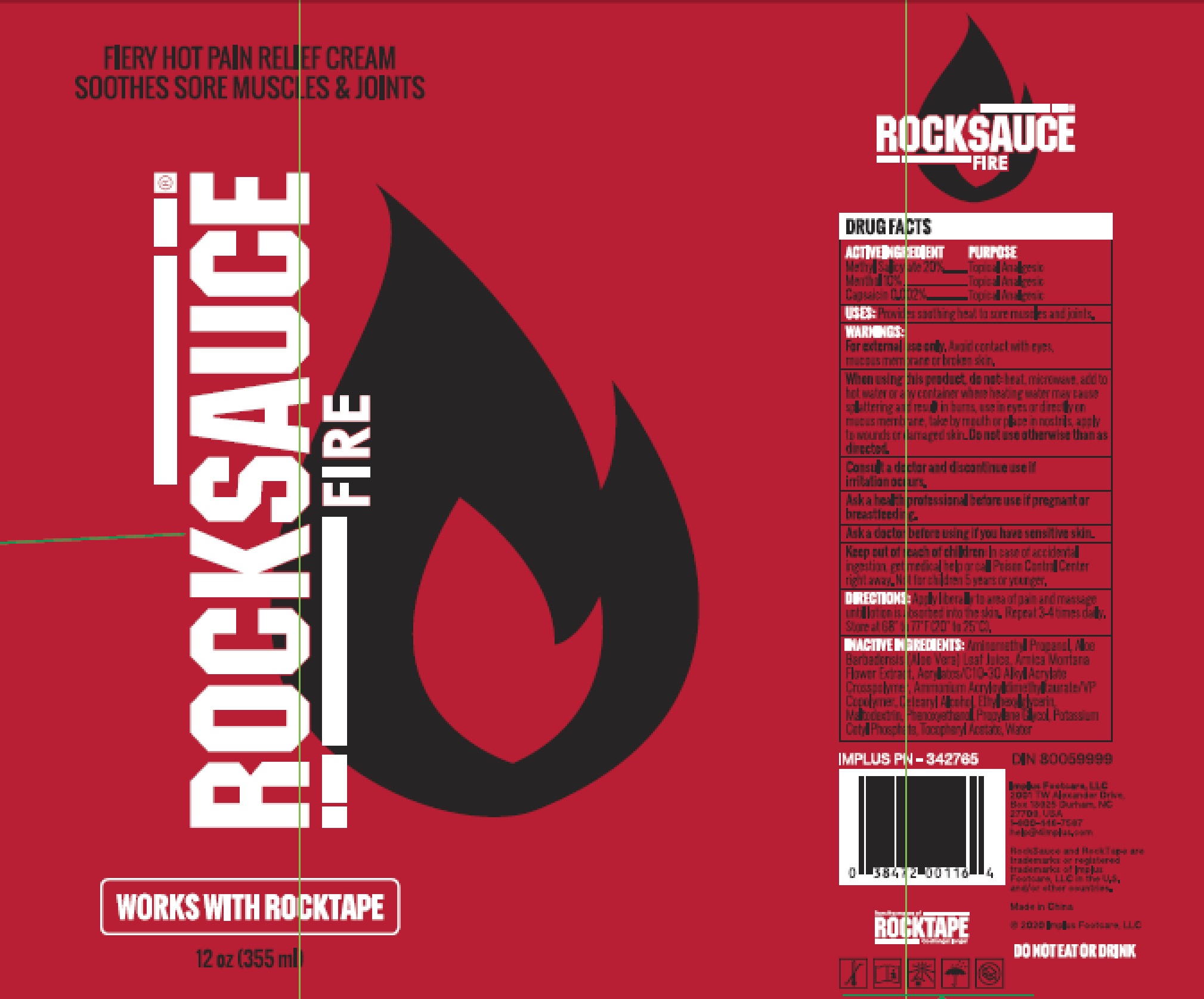 DRUG LABEL: RockSauce FIERY HOT PAIN RELIEF
NDC: 81683-112 | Form: CREAM
Manufacturer: Implus Footcare, LLC
Category: otc | Type: HUMAN OTC DRUG LABEL
Date: 20250407

ACTIVE INGREDIENTS: MENTHOL 36.2 g/355 mL; CAPSAICIN 0.00724 g/355 mL; METHYL SALICYLATE 72.4 g/355 mL
INACTIVE INGREDIENTS: AMMONIUM ACRYLOYLDIMETHYLTAURATE/VP COPOLYMER; ARNICA MONTANA FLOWER; ALOE VERA LEAF; CETOSTEARYL ALCOHOL; MALTODEXTRIN; ETHYLHEXYLGLYCERIN; WATER; PHENOXYETHANOL; PROPYLENE GLYCOL; POTASSIUM CETYL PHOSPHATE; .ALPHA.-TOCOPHEROL ACETATE; CARBOMER INTERPOLYMER TYPE A (ALLYL SUCROSE CROSSLINKED); AMINOMETHYLPROPANOL

81683-112

ACTIVE INGREDIENT

Methyl Salicylate 20%

Menthol 10%

Capsaicin0.002%

PURPOSE

Topical Analgesic

USES:

Provides soothing heat to sore muscles and joints.

WARNINGS:

For external use only. Avoid contact with eyes, mucous membrane or broken skin.

When using this product, do not:

heat, microwave, add to hot water or any container where heating water may cause splattering and result in burns, use in eyes or directly on mucus membrane, take by mouth or place in nostrils, apply to wounds or damaged skin.

Do not use otherwise than as directed.

ASK DOCTOR

Consult a doctor and discontinue use if irritation occurs.

Ask a health professional before use if pregnant or breastfeeding.

Ask a doctor before using if you have sensitive skin.

Keep out of reach of children:

In case of accidental ingestion, get medical help or call Poison Control Center right away. Not for children 5 years or younger.

DIRECTIONS:

Apply liberally to area of pain and massage until lotion is absorbed into the skin. Repeat 3-4 times daily. Store at 68° to 77 ℉(20° to 25℃).

INACTIVE INGREDIENTS:

Aminomethyl Propanol, Aloe Barbadensis(Aloe Vera)Leaf Juice, Arnica Montana Flower Extract, Acrylates/C10-30 Alkyl Acrylate Crosspolymer, Ammonium Acryloyldimethyltaurate/VP Copolymer, Cetearyl Alcohol, Ethylhexylglycerin, Maltodextrin, Phenoxyethanol, Propylene Glycol, Potassium Cetyl Phosphate, Tocopheryl Acetate, Water